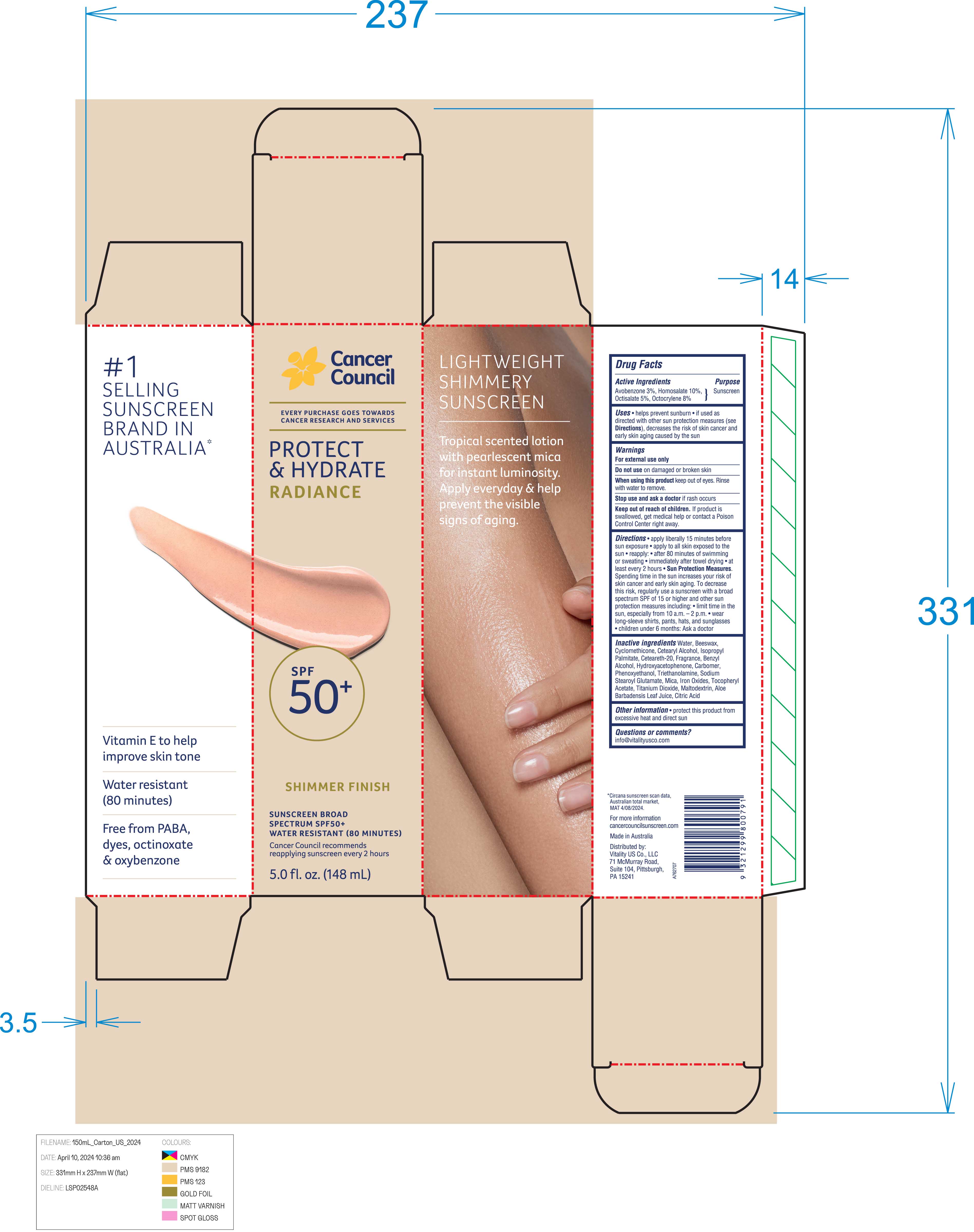 DRUG LABEL: Protect and Hydrate Radiance Sunscreen Broad Spectrum SPF 50
NDC: 70157-030 | Form: CREAM
Manufacturer: Baxter Laboratories Pty. Ltd.
Category: otc | Type: HUMAN OTC DRUG LABEL
Date: 20250908

ACTIVE INGREDIENTS: OCTOCRYLENE 8 g/100 mL; HOMOSALATE 10 g/100 mL; OCTISALATE 5 g/100 mL; AVOBENZONE 3 g/100 mL
INACTIVE INGREDIENTS: WATER; CETEARYL ALCOHOL; .ALPHA.-TOCOPHEROL ACETATE; ISOPROPYL PALMITATE; BENZYL ALCOHOL; TRIETHANOLAMINE; CITRIC ACID; CYCLOMETHICONE; BEESWAX; CARBOMER HOMOPOLYMER, UNSPECIFIED TYPE; CETEARETH-20; SODIUM STEAROYL GLUTAMATE; MICA; MALTODEXTRIN; ALOE BARBADENSIS LEAF JUICE; HYDROXYACETOPHENONE; PHENOXYETHANOL; TITANIUM DIOXIDE; FERROUS OXIDE

Protect and Hydrate Radiance Sunscreen Broad Spectrum SPF 50+

Active Ingredients Purpose

Avobenzone 3% Sunscreen

Homosalate 10%

Octisalate5%

Octocrylene 8%

Uses

- Helps prevent sunburn
- If used as directed with other sun protection measures (see Directions), decreases the risk of skin cancer and early skin aging caused by the sun.

Keep out of reach of children. If product is swallowed, get medical help or contact a Poison Control Center right away.

Stop use and ask a doctor if rash occurs

Warnings

For external use only

Do not use on damaged or broken skin

When using this product keep out of eyes. Rinse with water to remove.

DOSAGE AND ADMINISTRATION

Apply liberally 15 minutes before sun exposure.

apply to all skin exposed to the sun

reapply:

- 80 minutes of swimming or sweating
- immediately after towel drying
- at least every 2 hours

- Sun Protection Measures. Spending time in the sun increases your risk of skin cancer and early skin aging. To decrease this risk, regularly use a sunscreen with a Broad Spectrum SPF value of 15 or higher and other sun protection measures including:
- Limit time in the sun, especially from 10 a.m.- 2 p.m.
- Wear long-sleeved shirts, pants, hats, and sunglasses.
- Children under 6 months: Ask a doctor.

INACTIVE INGREDIENT

Water, Beeswax, Cyclomethicone, Cetearyl Alcohol, Isopropyl Palmitate, Ceteareth-20, Fragrance, Benzyl Alcohol, Hydroxyacetophenone, Carbomer, Phenoxyethanol, Triethanolamine, Sodium Stearoyl Glutamate, Mica, Iron Oxides, Tocopheryl Acetate, Titanium Dioxide, Maltodextrin, Aloe Barbadensis Leaf Juice, Citric

PACKAGE LABEL

Protect & Hydrate Radiance

Shimmer Finish

Sunscreen Broad Spectrum SPF 50+

Water Resistant (80 Minutes)

5.0 fl. oz. (148 mL)